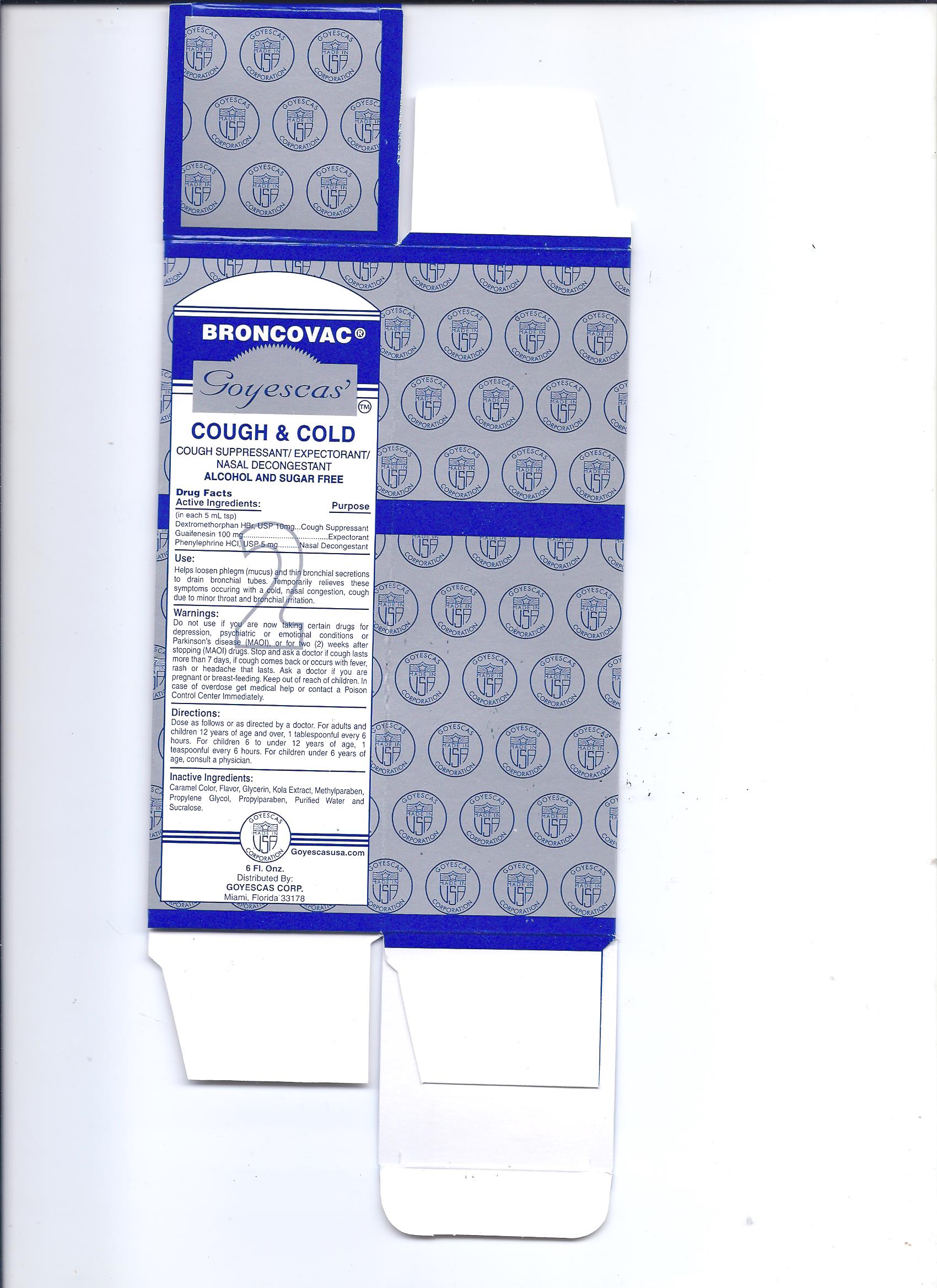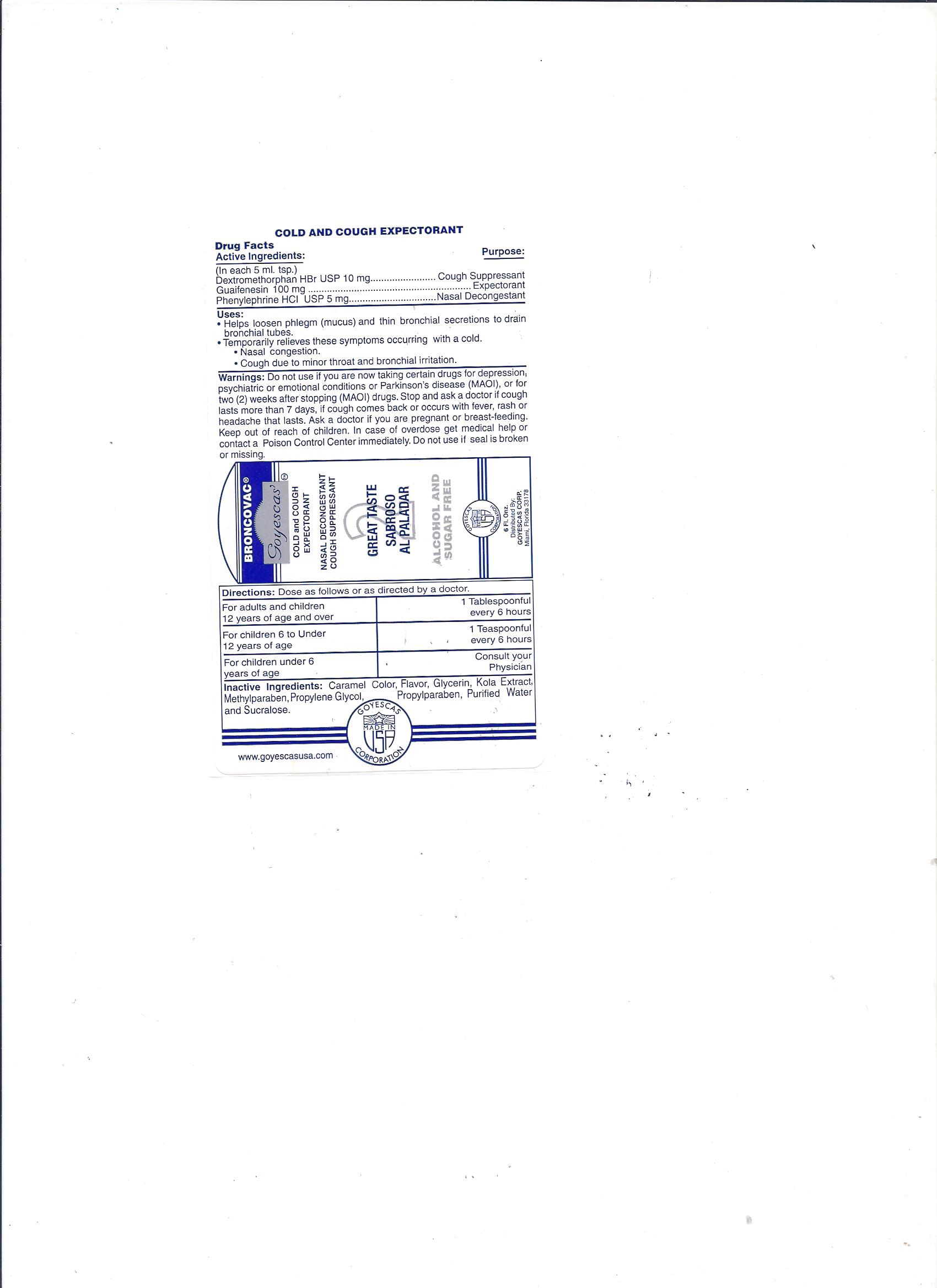 DRUG LABEL: Goyescas Broncovac 2
NDC: 11856-0017 | Form: LIQUID
Manufacturer: GOYESCAS OF FLA
Category: otc | Type: HUMAN OTC DRUG LABEL
Date: 20151019

ACTIVE INGREDIENTS: PHENYLEPHRINE HYDROCHLORIDE 5 mg/5 mL; GUAIFENESIN 100 mg/5 mL; DEXTROMETHORPHAN HYDROBROMIDE 10 mg/5 mL
INACTIVE INGREDIENTS: CARAMEL; GLYCERIN; METHYLPARABEN; PROPYLPARABEN; WATER; SUCRALOSE

Active Ingredient

Drug Facts

Active Ingredients: Purpose

(in each 5 ml. tsp)

Dextromethorphan HBr USP 10mg Cough Suppresant

Guaifenesin USP 100mg Expectorant

Phenylephrine HCI USP 5mg Nasal Decongestant

Dosage & Administration

Directions:

Dose as follows or as directed by a doctor. For adults and children 12 years of age and older, 1 tablespoonful every 6 hours. For children 6 to under 12 years of age, 1 teaspoonful every 6 hours. For children under 6 years of age, consult a Physician.

Warnings

Do not use if you are now taking certain drugs for depression, psychiatric or emotional conditions or Parkinson’s disease (MAOI) or for two (2) weeks after stopping (MAOI) drugs. Stop and ask a doctor if cough lasts more than 7 days, if cough comes back or occurs with fever, rash or headache that lasts. Ask a doctor if you are pregnant or breast-feeding. Keep out of reach of children. In case of overdose get medical help or contact a Poison Control Center Immediately.

Inactive Ingredients

Caramel Color, Flavor, Glycerin, Kola Extract, Methylparaben, Propylene Glycol, Propylparaben, Purified Water and sucralose.

Use

Helps loosen phlegm (mucus) and thin bronchial secretions to drain bronchial tubes. Temporarily relieves these symptoms occurring with a cold, nasal congestion, cough due to minor throat and bronchial irritation.

Purpose

Active Ingredients: Purpose

(in each 5 ml. tsp)

Dextromethorphan HBr USP 10mg Cough Suppresant

Guaifenesin USP 100mg Expectorant

Phenylephrine HCI USP 5mg Nasal Decongestant

Warnings

Do not use if you are now taking certain drugs for depression, psychiatric or emotional conditions or Parkinson’s disease (MAOI) or for two (2) weeks after stopping (MAOI) drugs. Stop and ask a doctor if cough lasts more than 7 days, if cough comes back or occurs with fever, rash or headache that lasts. Ask a doctor if you are pregnant or breast-feeding. Keep out of reach of children. In case of overdose get medical help or contact a Poison Control Center Immediately.

Drug Facts

Active Ingredients: Purpose

(in each 5 ml. tsp)

Dextromethorphan HBr USP 10mg Cough Suppresant

Guaifenesin USP 100mg Expectorant

Phenylephrine HCI USP 5mg Nasal Decongestant

USE:

Helps loosen phlegm (mucus) and thin bronchial secretions to drain bronchial tubes. Temporarily relieves these symptoms occurring with a cold, nasal congestion, cough due to minor throat and bronchial irritation.

Warnings:

Do not use if you are now taking certain drugs for depression, psychiatric or emotional conditions or Parkinson’s disease (MAOI) or for two (2) weeks after stopping (MAOI) drugs. Stop and ask a doctor if cough lasts more than 7 days, if cough comes back or occurs with fever, rash or headache that lasts. Ask a doctor if you are pregnant or breast-feeding. Keep out of reach children. In case of overdose get medical help or contact a Poison Control Center Immediately.

Directions:

Dose as follows or as directed by a doctor. For adults and children 12 years of age and older, 1 tablespoonful every 6 hours. For children 6 to under 12 years of age, 1 teaspoonful every 6 hours. For children under 6 years of age, consult a Physician.

Inactive ingredients:

Caramel Color, Flavor, Glycerin, Kola Extract, Methylparaben, Propylene Glycol, Propylparaben, Purified Water and sucralose

.